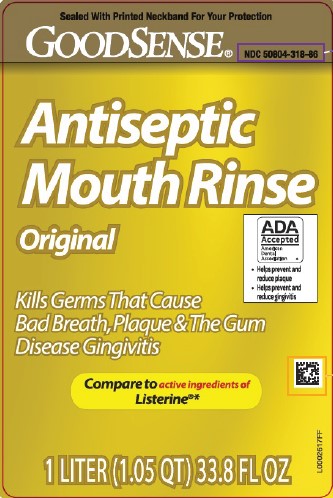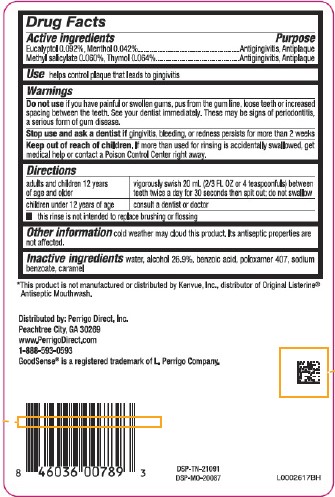 DRUG LABEL: Antiseptic
NDC: 50804-318 | Form: MOUTHWASH
Manufacturer: Perrigo Direct, Inc
Category: otc | Type: HUMAN OTC DRUG LABEL
Date: 20260219

ACTIVE INGREDIENTS: EUCALYPTOL 0.92 mg/1 mL; MENTHOL 0.42 mg/1 mL; METHYL SALICYLATE 0.6 mg/1 mL; THYMOL 0.64 mg/1 mL
INACTIVE INGREDIENTS: WATER; ALCOHOL; BENZOIC ACID; POLOXAMER 407; SODIUM BENZOATE; CARAMEL

Good Sense 318.003/318AH-AI
Antiseptic Mouthrinse

Active ingredients

Eucalyptol 0.092%

Menthol 0.042%

Methyl saliclate 0.060%

Thymol 0.064%

Purpose

Antigingivitis, Antiplaque

Use

helps control plaque that leads to gingivitis

Warnings

for this product

Do not use

if you have painful or swollen gums, pus from the gum line, loose teeth or increased spacing between the teeth. See your dentist immediately. These may be signs of periodontitis, a serous form of gum disease.

Stop use and ask a dentist if

gingivitis, bleeding or redness persists for more than 2 weeks

Keep out of reach of children.

If more than used for rinsing is accidentally swallowed, get medical help or contact a Poison Control Center right away.

Directions

adults and children 12 years of age and older - vigorously swish 20 mL (2/3 FL OZ or 4 teaspoonsfuls) between teeth twice a day for 30 seconds then spit out; do not swallow

children under 12 years of age - consult a dentist or doctor

- this rinse is not intended to replace brushing or flossing

Other information

cold weather may cloud this product. Its antiseptic properties are not affected.

Inactive ingredients

water, alcohol 26.9%, benzoic acid, poloxamer 407, sodium benzoate, caramel

Disclaimer

*This product is not manufactured or distributed by Kenvue, Inc., distributor of ListerineAntiseptic Mouthwash.

ADVERSE REACTION

Distributed by: Perrigo Direct, Inc.

Peachtree City, GA 30269

www.PerrigoDirect.com

1-888-593-0593

GoodSense®is a registered trademark of L. Perrigo Company.

DSP-TN-21091

DSP-MO-20087

Principal display panel

Sealed With Printed Neckband For Your Protection

GoodSense®

NDC 50804-318-86

Antiseptic

Mouth Rinse

Original

Kills Germs That Cause Bad Breath, Plaque & The Gum Disease Gingivitis

ADA Accepted

American Dental Association

• Helps prevent and reduce plaque
• Helps prevent and reduce gingivitis

Compare to active ingredients of Listerine®*

1 Liter (1.05 QT) 33.8 FL OZ